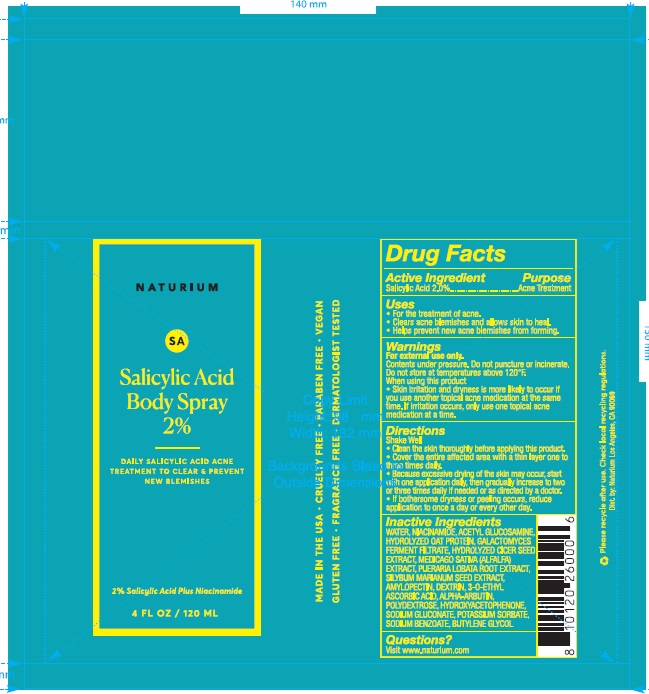 DRUG LABEL: Naturium Salicylic Acid Body 2%
NDC: 76354-124 | Form: AEROSOL, SPRAY
Manufacturer: e.l.f. Cosmetics, Inc
Category: otc | Type: HUMAN OTC DRUG LABEL
Date: 20251114

ACTIVE INGREDIENTS: SALICYLIC ACID 20 mg/1 mL
INACTIVE INGREDIENTS: PUERARIA MONTANA VAR. LOBATA ROOT; AMYLOPECTIN, UNSPECIFIED SOURCE; MEDICAGO SATIVA WHOLE; SILYBUM MARIANUM SEED; 3-O-ETHYL ASCORBIC ACID; ICODEXTRIN; SODIUM GLUCONATE; POTASSIUM SORBATE; SODIUM BENZOATE; N-ACETYLGLUCOSAMINE; HYDROXYACETOPHENONE; NIACINAMIDE; BUTYLENE GLYCOL; WATER; ALPHA-ARBUTIN

Naturium Salicylic Acid Body Spray 2%

Active Ingredient

Salicylic Acid 2.0%

Purpose

Acne Treatment

Uses

- For the treatment of acne.
- Clears acne blemishes and allows skin to heal.
- Helps prevent new acne blemishes from forming.

Warnings

For external use only.

Contents under pressure. Do not puncture or incinerate. Do not store at temperatures above 120F.

When using this product

- Skin irritation and dryness is more likely to occur if you use another topical acne medication at the same time. If irritation occurs, only use one topical acne medication at a time.

Directions

Shake Well

- Clean the skin thoroughly before applying this product.
- Cover the entire affected area with a thin layer one to three times daily.
- Because excessive drying of the skin may occur, start with one application daily, then gradually increase to two or three times daily if needed or as directed by a doctor.
- If bothersome dryness or peeling occurs, reduce application to once a day or every other day.

Inactive Ingredients

WATER, NIACINAMIDE, ACETYL GLUCOSAMINE, HYDROLYZED OAT PROTEIN, GALACTOMYCES FERMENT FILTRATE, HYDROLYZED CICER SEED EXTRACT, MEDICAGO SATIVA (ALFALFA) EXTRACT, PUERARIA LOBATA ROOT EXTRACT, SILYBUM MARIANUM SEED EXTRACT, AMYLOPECTIN, DEXTRIN, 3-O-ETHYL ASCORBIC ACID, ALPHA-ARBUTIN, POLYDEXTROSE, HYDROXYACETOPHENONE, SODIUM GLUCONATE, POTASSIUM SORBATE, SODIUM BENZOATE, BUTYLENE GLYCOL

Questions?

Visit www.naturium.com